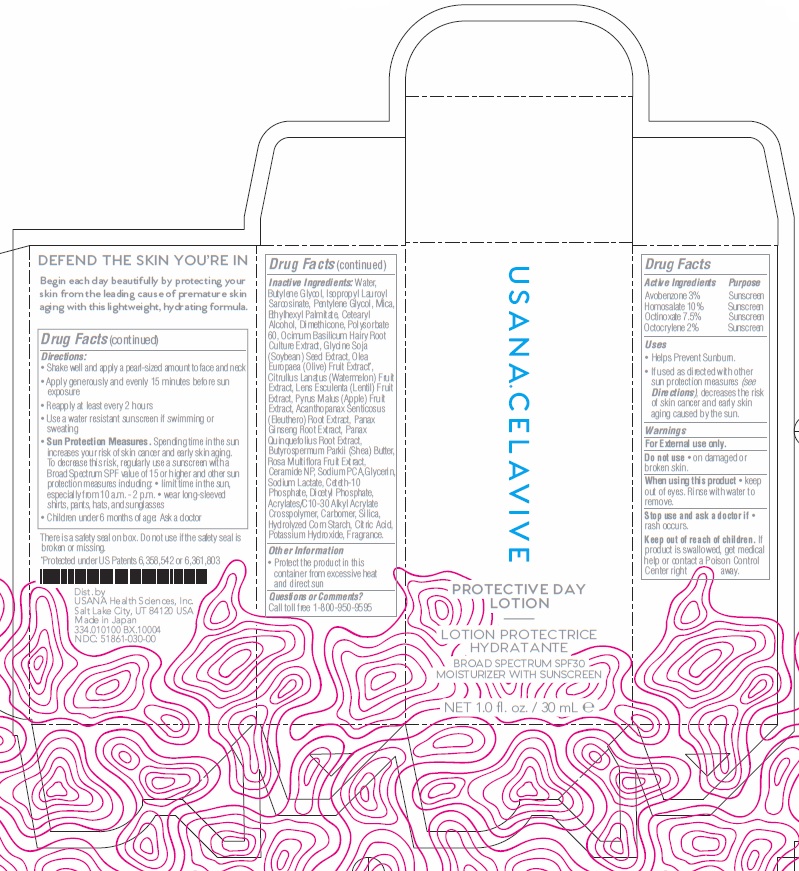 DRUG LABEL: Protective Day
NDC: 51861-060 | Form: LOTION
Manufacturer: USANA Health Sciences, Inc.
Category: otc | Type: HUMAN OTC DRUG LABEL
Date: 20231019

ACTIVE INGREDIENTS: AVOBENZONE 30 mg/1 mL; HOMOSALATE 100 mg/1 mL; OCTINOXATE 75 mg/1 mL; OCTOCRYLENE 20 mg/1 mL
INACTIVE INGREDIENTS: WATER; BUTYLENE GLYCOL; ISOPROPYL LAUROYL SARCOSINATE; PENTYLENE GLYCOL; MICA; ETHYLHEXYL PALMITATE; CETOSTEARYL ALCOHOL; DIMETHICONE; POLYSORBATE 60; SOYBEAN; BLACK OLIVE; WATERMELON; LENS CULINARIS FRUIT; APPLE; ELEUTHERO; ASIAN GINSENG; AMERICAN GINSENG; SHEA BUTTER; ROSA MULTIFLORA FRUIT; CERAMIDE NP; SODIUM PYRROLIDONE CARBOXYLATE; GLYCERIN; SODIUM LACTATE; CETETH-10 PHOSPHATE; DIHEXADECYL PHOSPHATE; CARBOMER INTERPOLYMER TYPE A (ALLYL SUCROSE CROSSLINKED); CARBOXYPOLYMETHYLENE; SILICON DIOXIDE; CITRIC ACID MONOHYDRATE; POTASSIUM HYDROXIDE

Protective Day Lotion

Active Ingredients

Avobenzone 3% Homosalate 10% Octinoxate 7.5% Octocrylene 2%

Purpose

Sunscreen Sunscreen Sunscreen Sunscreen

Uses

• Helps Prevent Sunburn. • If used as directed with other sun protection measures (see Directions), decreases the risk of skin cancer and early skin aging caused by the sun.

Warnings

• on damaged or broken skin. • keep out of eyes. Rinse with water to remove. • rash occurs. For External use only. Do not use When using this product Stop use and ask a doctor if

Keep out of reach of children.

If product is swallowed, get medical help or contact a Poison Control Center right away.

DOSAGE AND ADMINISTRATION

• Shake well and apply a pearl-sized amount to face and neck • Apply generously and evenly 15 minutes before sun exposure • Reapply at least every 2 hours • Use a water resistant sunscreen if swimming or sweating • . Spending time in the sun increases your risk of skin cancer and early skin aging. To decrease this risk, regularly use a sunscreen with a Broad Spectrum SPF value of 15 or higher and other sun protection measures including: • limit time in the sun, especially from 10 a.m. - 2 p.m. • wear long-sleeved shirts, pants, hats, and sunglasses • Children under 6 months of age: Ask a doctor
Sun Protection Measures

Inactive Ingredients:

Water, Butylene Glycol, Isopropyl Lauroyl Sarcosinate, Pentylene Glycol, Mica, Ethylhexyl Palmitate, Cetearyl Alcohol, Dimethicone, Polysorbate 60, Ocimum Basilicum Hairy Root Culture Extract, Glycine Soja (Soybean) Seed Extract, Olea Europaea (Olive) Fruit Extract, Citrullus Lanatus (Watermelon) Fruit Extract, Lens Esculenta (Lentil) Fruit Extract, Pyrus Malus (Apple) Fruit Extract, Acanthopanax Senticosus (Eleuthero) Root Extract, Panax Ginseng Root Extract, Panax Quinquefolius Root Extract, Butyrospermum Parkii (Shea) Butter, Rosa Multiflora Fruit Extract, Ceramide NP, Sodium PCA,Glycerin, Sodium Lactate, Ceteth-10 Phosphate, Dicetyl Phosphate, Acrylates/C10-30 Alkyl Acrylate Crosspolymer, Carbomer, Silica, Hydrolyzed Corn Starch, Citric Acid, Potassium Hydroxide, Fragrance.

Other Information

• Protect the product in this container from excessive heat and direct sun

Questions or Comments?

Call toll free 1-800-950-9595